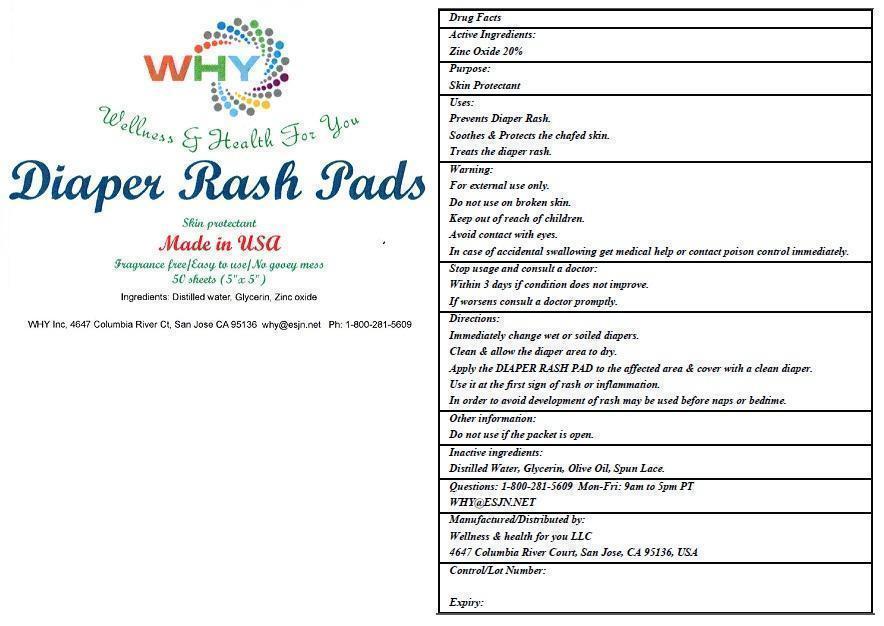 DRUG LABEL: WHY Diaper Rash Pads
NDC: 60939-101 | Form: CLOTH
Manufacturer: WELLNESS AND HEALTH FOR YOU LLC
Category: otc | Type: HUMAN OTC DRUG LABEL
Date: 20150123

ACTIVE INGREDIENTS: ZINC OXIDE 20 g/100 g
INACTIVE INGREDIENTS: WATER; GLYCERIN; OLIVE OIL

WHY Diaper Rash Pads

Active Ingredients:

Zinc Oxide 20%

Purpose:

Skin Protectant

Keep out of reach of children.

Uses:

Prevents Diaper Rash.
Soothes & Protects the chafed skin.
Treats the diaper rash.

Warning:

For external use only.
Do not use on broken skin.
Avoid contact with eyes.
In case of accidental swallowing get medical help or contact poison control immediately.

Stop usage and consult a doctor:
Within 3 days if condition does not improve.
If worsens consult a doctor promptly.

Directions:

Immediately change wet or soiled diapers.
Clean & allow the diaper area to dry.
Apply the DIAPER RASH PAD to the affected area & cover with a clean diaper.
Use it at the first sign of rash or inflammation.
In order to avoid development of rash may be used before naps or bedtime.

Other information:

Do not use if the packet is open.

Inactive ingredients:

Distilled Water, Glycerin, Olive oil, Spun Lace.

QUESTIONS

Questions: 1-800-281-5609 Mon-Fri: 9am to 5pm PT

WHY@ESJN.NET

Manufactured/Distributed by:
Wellness & health for you LLC
4647 Columbia River Court, San Jose, CA 95136, USA.